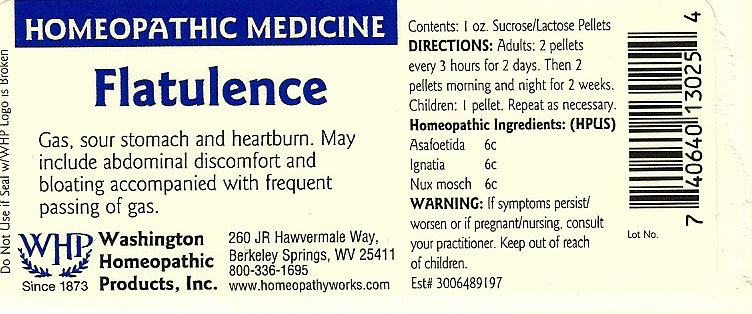 DRUG LABEL: Flatulence
NDC: 68428-007 | Form: PELLET
Manufacturer: Washington Homeopathic Products
Category: homeopathic | Type: HUMAN OTC DRUG LABEL
Date: 20191223

ACTIVE INGREDIENTS: FERULA ASSA-FOETIDA RESIN 6 [hp_C]/28 g; STRYCHNOS IGNATII SEED 6 [hp_C]/28 g; NUTMEG 6 [hp_C]/28 g
INACTIVE INGREDIENTS: SUCROSE; LACTOSE

DRUG FACTS

ACTIVE INGREDIENTS

ASAFOETIDA 6C

IGNATIA 6C

NUX MOSCH 6C

USES

To relieve the symptoms of gas, sour stomach and heartburn. May include abdominal discomfort and bloating accompanied with frequent passing of gas.

KEEP OUT OF REACH OF CHILDREN

Keep this and all medicines out of reach of children.

INDICATIONS

ASAFOETIDA Flatulence

IGNATIA Sadness

NUX MOSCH Dry mouth

STOP USE AND ASK DOCTOR

If symptoms persist/worsen or if pregnant/nursing, stop use and consult your practitioner.

DIRECTIONS

Adults 2 pellets every 3 hours for 2 days. Then 2 pellets morning and night for 2 weeks.

Children: 1 pellet. Repeat as necessary.

INACTIVE INGREDIENTS

Sucrose/Lactose

PRINCIPAL DISPLAY PANEL

Enter section text here